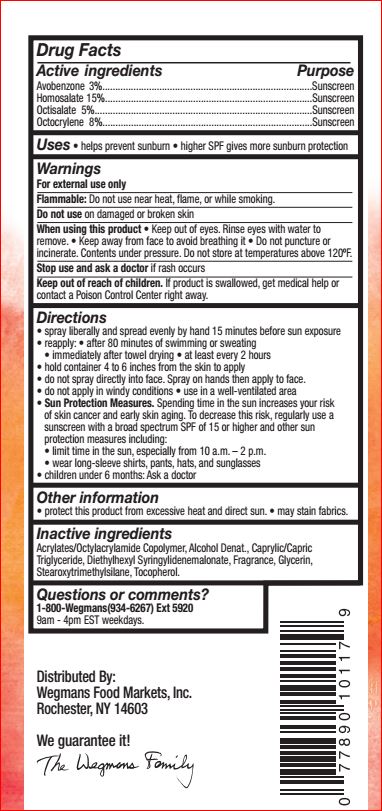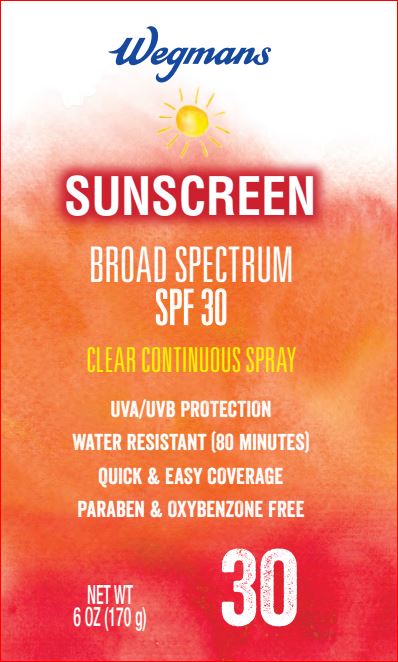 DRUG LABEL: Sunscreen SPF 30
NDC: 47124-440 | Form: SPRAY
Manufacturer: Wegman
Category: otc | Type: HUMAN OTC DRUG LABEL
Date: 20180111

ACTIVE INGREDIENTS: Avobenzone 3 g/100 mL; Homosalate 15 g/100 mL; Octisalate 5 g/100 mL; Octocrylene 8 g/100 mL
INACTIVE INGREDIENTS: Alcohol; MEDIUM-CHAIN TRIGLYCERIDES; Diethylhexyl Syringylidenemalonate; Glycerin; Stearoxytrimethylsilane; Tocopherol

Drug Facts

Active ingredients Purpose

Avobenzone 3%...........................Sunscreen
Homosalate 15%..........................Sunscreen
Octisalate 5%.......................... ....Sunscreen
Octocrylene 8%............................Sunscreen

INDICATIONS AND USAGE

Uses • helps prevent sunburn

Warnings

For external use only
Do not use on damaged or broken skin
When using this product keep out of eyes. Rinse with water to remove.
Stop use and ask a doctor if rash occurs
Keep out of reach of children. If product is swallowed, get medical help or contact a Poison Control Center right away.

Directions

• apply liberally 15 minutes before sun exposure
• reapply: • after 80 minutes of swimming or sweating
• immediately after towel drying • at least every 2 hours
• Sun Protection Measures. Spending time in the sun
increases your risk of skin cancer and early skin aging.
To decrease this risk, regularly use a sunscreen with a
broad spectrum SPF of 15 or higher and other sun
protection measures including:
• limit time in the sun, especially from 10 a.m. – 2 p.m.
• wear long-sleeve shirts, pants, hats, and sunglasses
• children under 6 months: Ask a doctor

Inactive ingredients

Acrylates/C10-30 Alkyl Acrylate Crosspolymer, Benzyl Alcohol, Caprylic/Capric Triglyceride, Chlorphenesin, Diethylhexyl Syringylidenemalonate, Disodium EDTA, Ethylhexyl Palmitate, Fragrance, Oleth-3, Polyamide-8, Sodium Ascorbyl Phosphate, Sorbitol, Tocopherol, Triethanolamine, Water.

Other information

• protect this product from excessive heat and direct sun • may stain fabrics.

Questions or comments?

1-800-Wegmans(934-6267) Ext 5920
9am - 4pm EST weekdays.